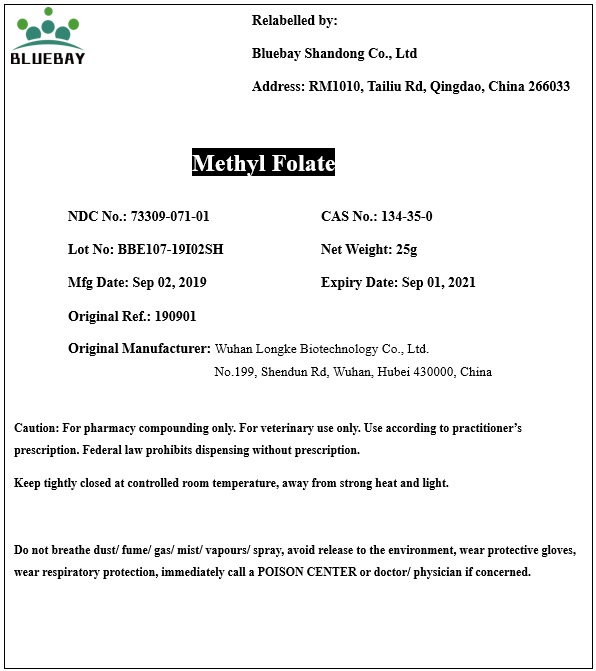 DRUG LABEL: Methyl Folate
NDC: 73309-071 | Form: POWDER
Manufacturer: BLUEBAY SHANDONG CO.,LTD
Category: other | Type: BULK INGREDIENT
Date: 20191218

ACTIVE INGREDIENTS: 5-METHYLTETRAHYDROFOLIC ACID 1 g/1 g

Methyl Folate